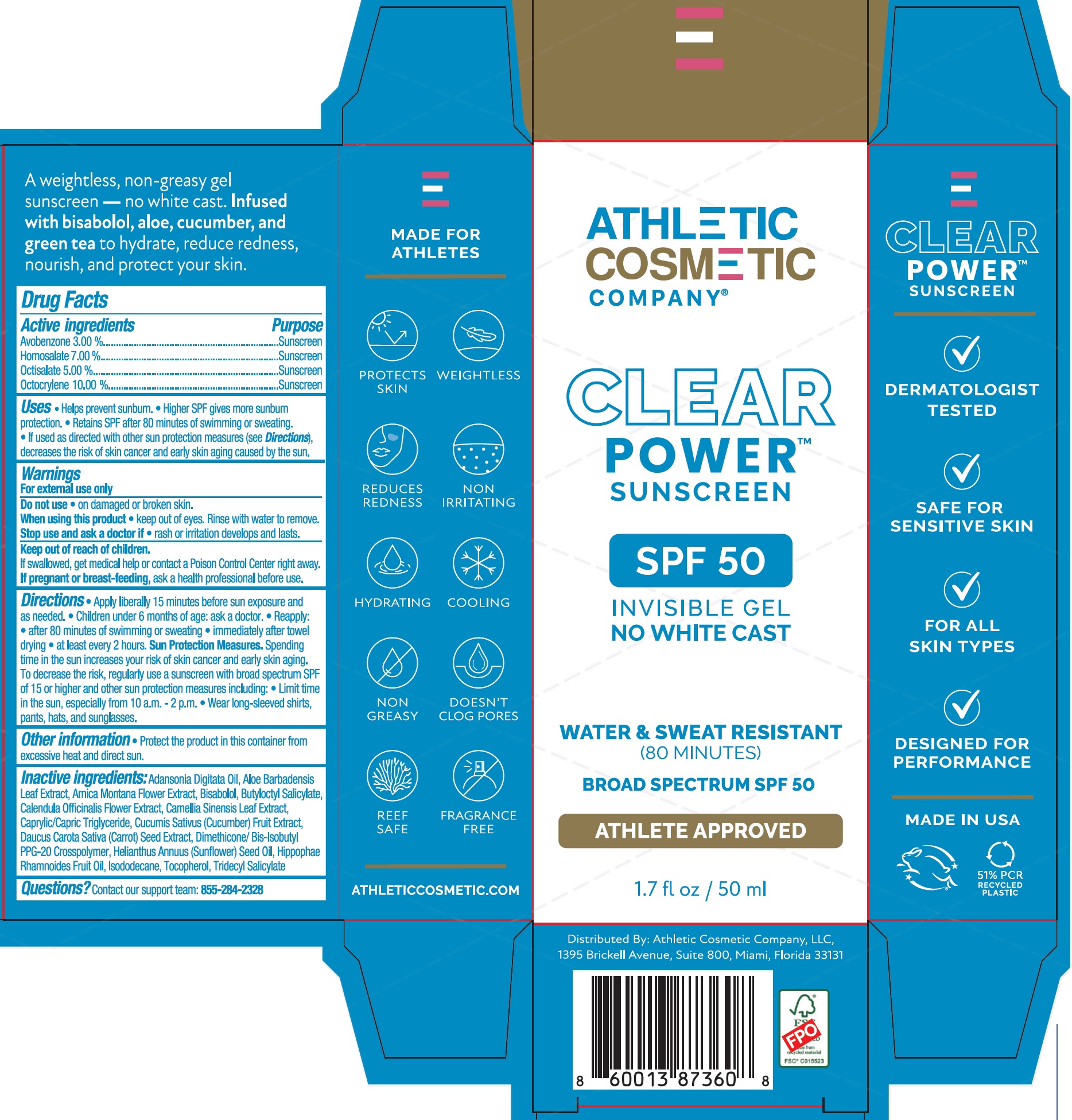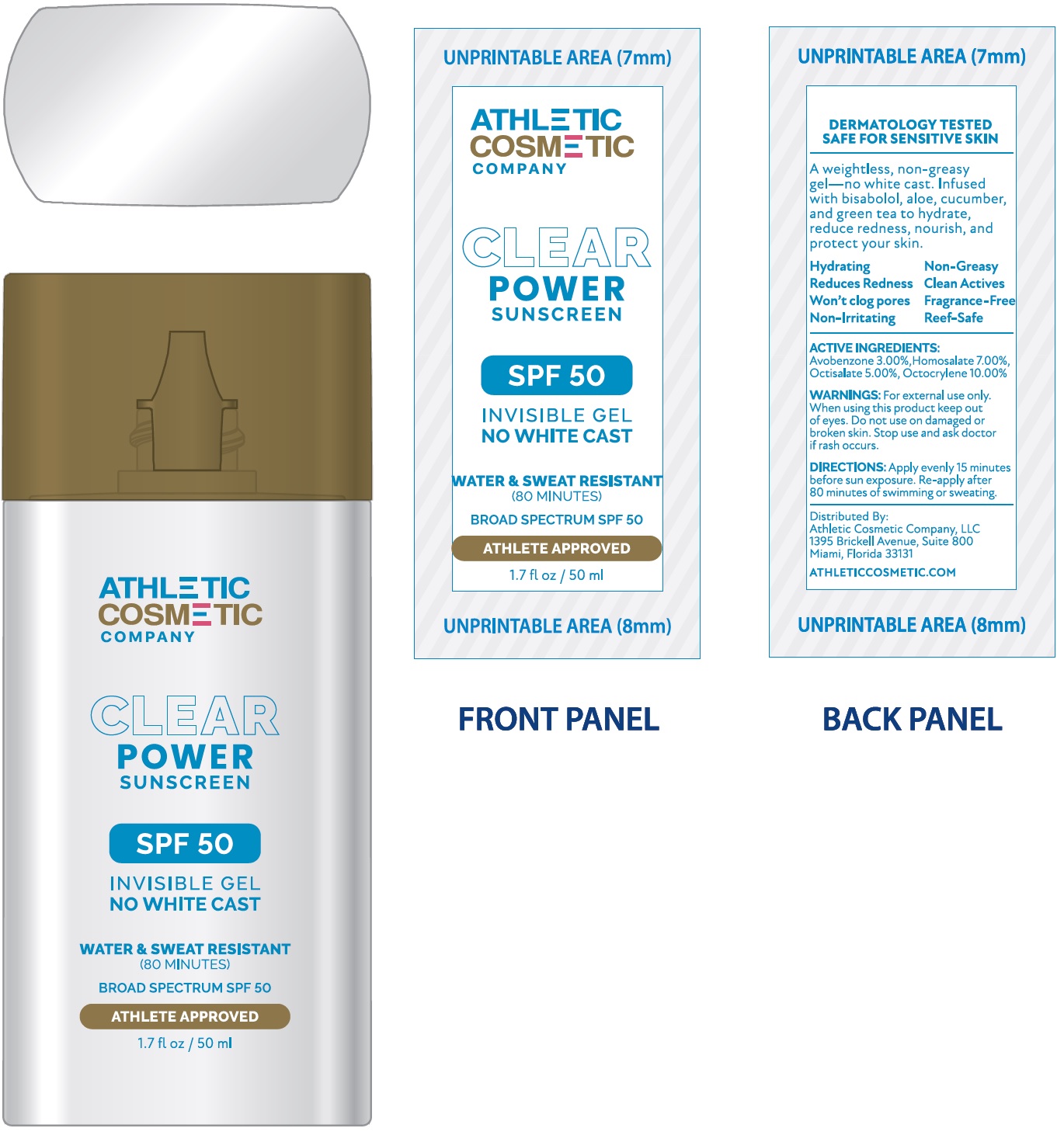 DRUG LABEL: ATHLETIC COSMETIC COMPANY Clear Power Sunscreen SPF 50
NDC: 85927-626 | Form: GEL
Manufacturer: ATHLETIC COSMETIC COMPANY LLC
Category: otc | Type: HUMAN OTC DRUG LABEL
Date: 20250710

ACTIVE INGREDIENTS: AVOBENZONE 30 mg/1 mL; HOMOSALATE 70 mg/1 mL; OCTISALATE 50 mg/1 mL; OCTOCRYLENE 100 mg/1 mL
INACTIVE INGREDIENTS: ADANSONIA DIGITATA SEED OIL; ALOE VERA LEAF JUICE; ARNICA MONTANA FLOWER; LEVOMENOL; BUTYLOCTYL SALICYLATE; CALENDULA OFFICINALIS FLOWER; GREEN TEA LEAF; MEDIUM-CHAIN TRIGLYCERIDES; CUCUMBER; DAUCUS CAROTA SUBSP. SATIVUS SEED; DIMETHICONE/BIS-ISOBUTYL PPG-20 CROSSPOLYMER; SUNFLOWER OIL; HIPPOPHAE RHAMNOIDES FRUIT OIL; ISODODECANE; TOCOPHEROL; TRIDECYL SALICYLATE

ATHLETIC COSMETIC COMPANY Clear Power Sunscreen SPF 50

Active ingredients

Avobenzone 3.00%
Homosalate 7.00%
Octisalate 5.00%
Octocrylene 10.00%

Purpose

Sunscreen

Uses

• Helps prevent sunburn.
• Higher SPF gives more sunburn protection.
• Retains SPF after 80 minutes of swimming or sweating.
• If used as directed with other sun protection measures (see Directions), decreases the risk of skin cancer and early skin aging caused by the sun.

Warnings

For external use only

Do not use

- on damaged or broken skin.

When using this product

- keep out of eyes. Rinse with water to remove.

Stop use and ask a doctor if

- rash or irritation develops and lasts.

Keep out of reach of children.

If swallowed, get medical help or contact a Poison Control Center right away.

If pregnant or breast-feeding,

ask a health professional before use.

Directions

• Apply liberally 15 minutes before sun exposure and as needed.
• Children under 6 months of age: ask a doctor.
• Reapply:
• after 80 minutes of swimming or sweating
• immediately after towel drying
• at least every 2 hours.
• Sun Protection Measures.Spending time in the sun increases your risk of skin cancer and early skin aging. To decrease the risk, regularly use a sunscreen with broad spectrum SPF of 15 or higher and other sun protection measures including:
• Limit time in the sun, especially from 10 a.m.-2 p.m.
• Wear long-sleeved shirts, pants, hats, and sunglasses.

Other information

- Protect the product in this container from excessive heat and direct sun.

Inactive ingredients:

Adansonia Digitata Oil, Aloe Barbadensis Leaf Extract, Arnica Montana Flower Extract, Bisabolol, Butyloctyl Salicylate, Calendula Officinalis Flower Extract, Camellia Sinensis Leaf Extract, Caprylic/Capric Triglyceride, Cucumis Sativus (Cucumber) Fruit Extract, Daucus Carota Sativa (Carrot) Seed Extract, Dimethicone/ Bis-Isobutyl PPG-20 Crosspolymer, Helianthus Annuus (Sunflower) Seed Oil, Hippophae Rhamnoides Fruit Oil, Isododecane, Tocopherol, Tridecyl Salicylate

Questions?

Contact our support team: 855-284-2328